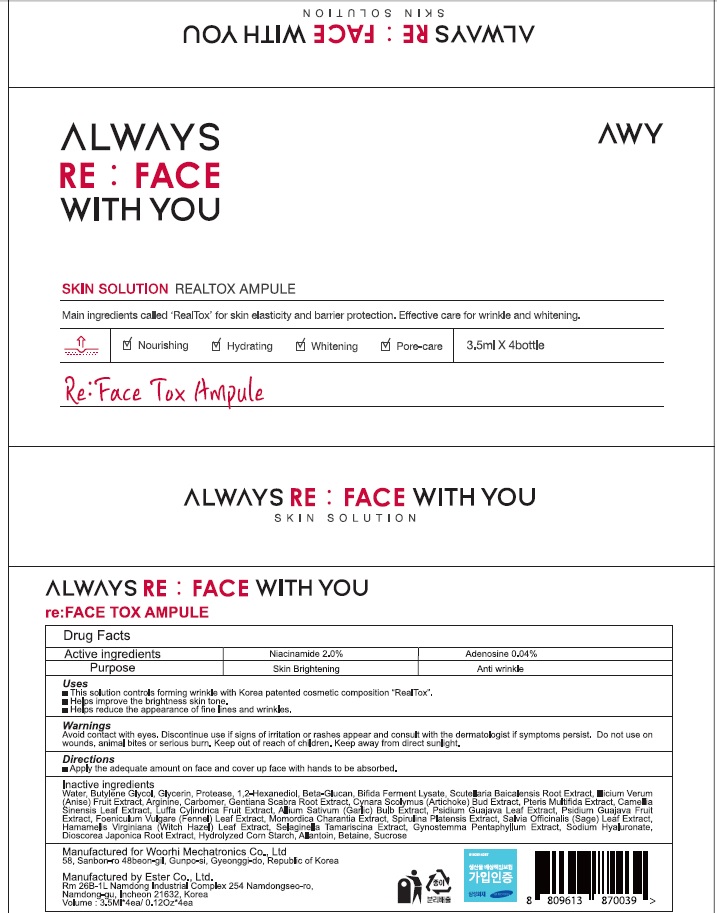 DRUG LABEL: reFACE TOX AMPULE
NDC: 72729-030 | Form: SOLUTION
Manufacturer: Woorhi Mechatronics Co., Ltd.
Category: otc | Type: HUMAN OTC DRUG LABEL
Date: 20210628

ACTIVE INGREDIENTS: Niacinamide 0.07 g/3.5 mL; Adenosine 0.001 g/3.5 mL
INACTIVE INGREDIENTS: Water; Butylene Glycol

ACTIVE INGREDIENTS

Niacinamide 2.0%, Adenosine 0.04%

INACTIVE INGREDIENTS

Water, Butylene Glycol, Glycerin, Protease, 1,2-Hexanediol, Beta-Glucan, Bifida Ferment Lysate, Scutellaria Baicalensis Root Extract, Illicium Verum (Anise) Fruit Extract, Arginine, Carbomer, Gentiana Scabra Root Extract, Cynara Scolymus (Artichoke) Bud Extract, Pteris Multifida Extract, Camellia Sinensis Leaf Extract, Luffa Cylindrica Fruit Extract, Allium Sativum (Garlic) Bulb Extract, Psidium Guajava Leaf Extract, Psidium Guajava Fruit Extract, Foeniculum Vulgare (Fennel) Leaf Extract, Momordica Charantia Extract, Spirulina Platensis Extract, Salvia Officinalis (Sage) Leaf Extract, Hamamelis Virginiana (Witch Hazel) Leaf Extract, Selaginella Tamariscina Extract, Gynostemma Pentaphyllum Extract, Sodium Hyaluronate, Dioscorea Japonica Root Extract, Hydrolyzed Corn Starch, Allantoin, Betaine, Sucrose

PURPOSE

Skin Brightening, Anti Wrinkle

WARNINGS

Avoid contact with eyes.
Discontinue use if signs of irritation or rashes appear and consult with the dermatologist if symptoms persist.
Do not use on wounds, animal bites or serious burn.
Keep out of reach of children.
Keep away from direct sunlight.

KEEP OUT OF REACH OF CHILDREN

Uses

■ This solution controls forming wrinkle with Korea patented cosmetic composition “RealTox”.
■ Helps improve the brightness skin tone
■ Helps reduce the appearance of fine lines and wrinkles

Directions

■ Apply the adequate amount on face and cover up face with hands to be absorbed